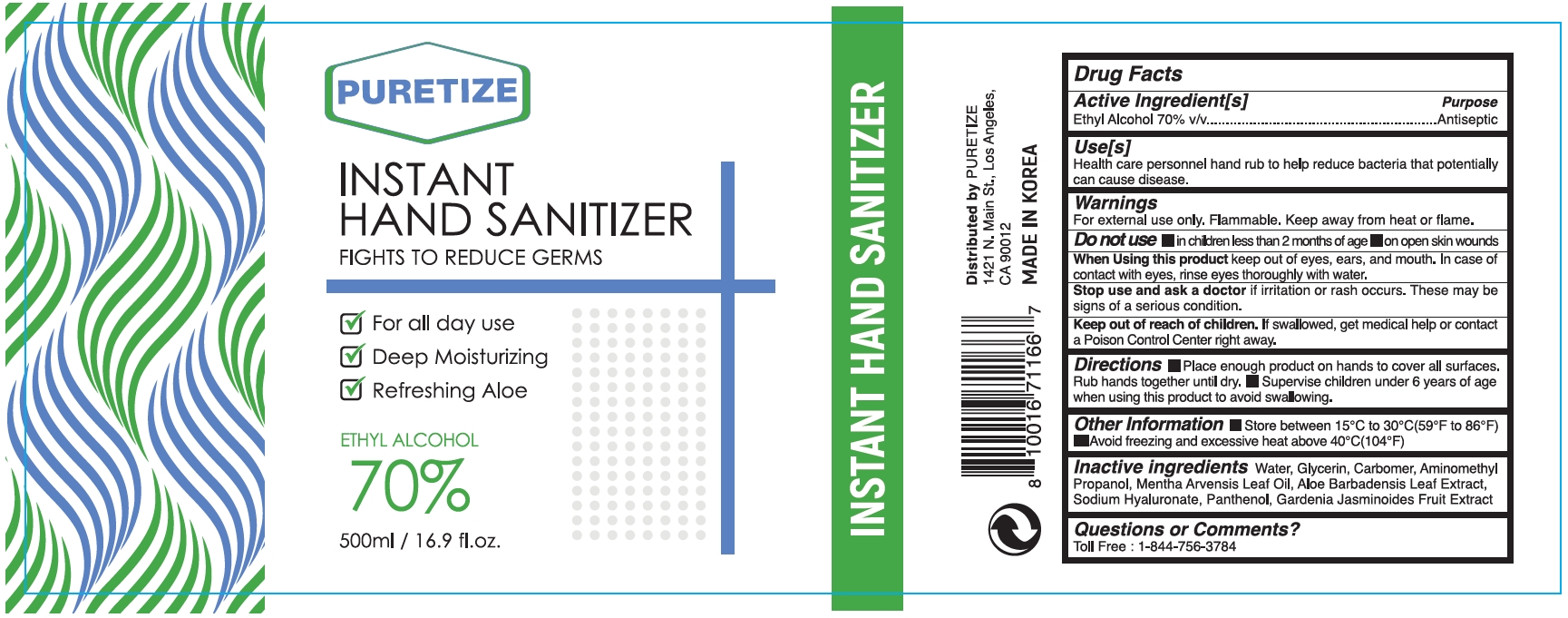 DRUG LABEL: Puretize Instant Hand Sanitizer 500ml
NDC: 76887-102 | Form: GEL
Manufacturer: ARGO KOREA Co., Ltd
Category: otc | Type: HUMAN OTC DRUG LABEL
Date: 20200528

ACTIVE INGREDIENTS: ALCOHOL 70 mL/100 mL
INACTIVE INGREDIENTS: WATER; ALOE VERA LEAF; GLYCERIN; MENTHA ARVENSIS LEAF OIL; CARBOMER 940; AMINOMETHYLPROPANOL; HYALURONATE SODIUM; PANTHENOL; GARDENIA JASMINOIDES FRUIT

PURETIZE INSTANT HAND SANITIZER 70% 500ml

Active Ingredient(s)

Alcohol 70% v/v. Purpose: Antiseptic

Purpose

Antiseptic, Hand Sanitizer

Use

Health care personnel hand rub to help reduce bacteria that potentially can cause disease.

Warnings

For external use only. Flammable. Keep away from heat or flame

Do not use

- in children less than 2 months of age
- on open skin wounds

When using

When using this product keep out of eyes, ears, and mouth. In case of contact with eyes, rinse eyes thoroughly with water.

Stop use

Stop use and ask a doctor if irritation or rash occurs. These may be signs of a serious condition.

Keep out of reach of children. If swallowed, get medical help or contact a Poison Control Center right away.

Directions

- Place enough product on hands to cover all surfaces. Rub hands together until dry.
- Supervise children under 6 years of age when using this product to avoid swallowing.

Other information

- Store between 15-30C (59-86F)
- Avoid freezing and excessive heat above 40C (104F)

Inactive ingredients

Water, Glycerin, Carbomer, Aminomethyl Propanol, Mentha Arvensis Leaf Oil, Aloe Barbdensis Leaf Extract, Sodium Hyaluronate, Panthenol, Gardenia Jasminoides Fruit Extract

Questions or Comments?

Toll Free: 1-844-756-3784

Package Label - Principal Display Panel

PURETIZE
INSTANT
HAND SANITIZER
FIGHTS TO REDUCE GERMS,
For all day use,
Deep Moisturizing, Refreshing Aloe,
ETHYL ALCOHOL
70%
500ml / 16.9fl.oz.